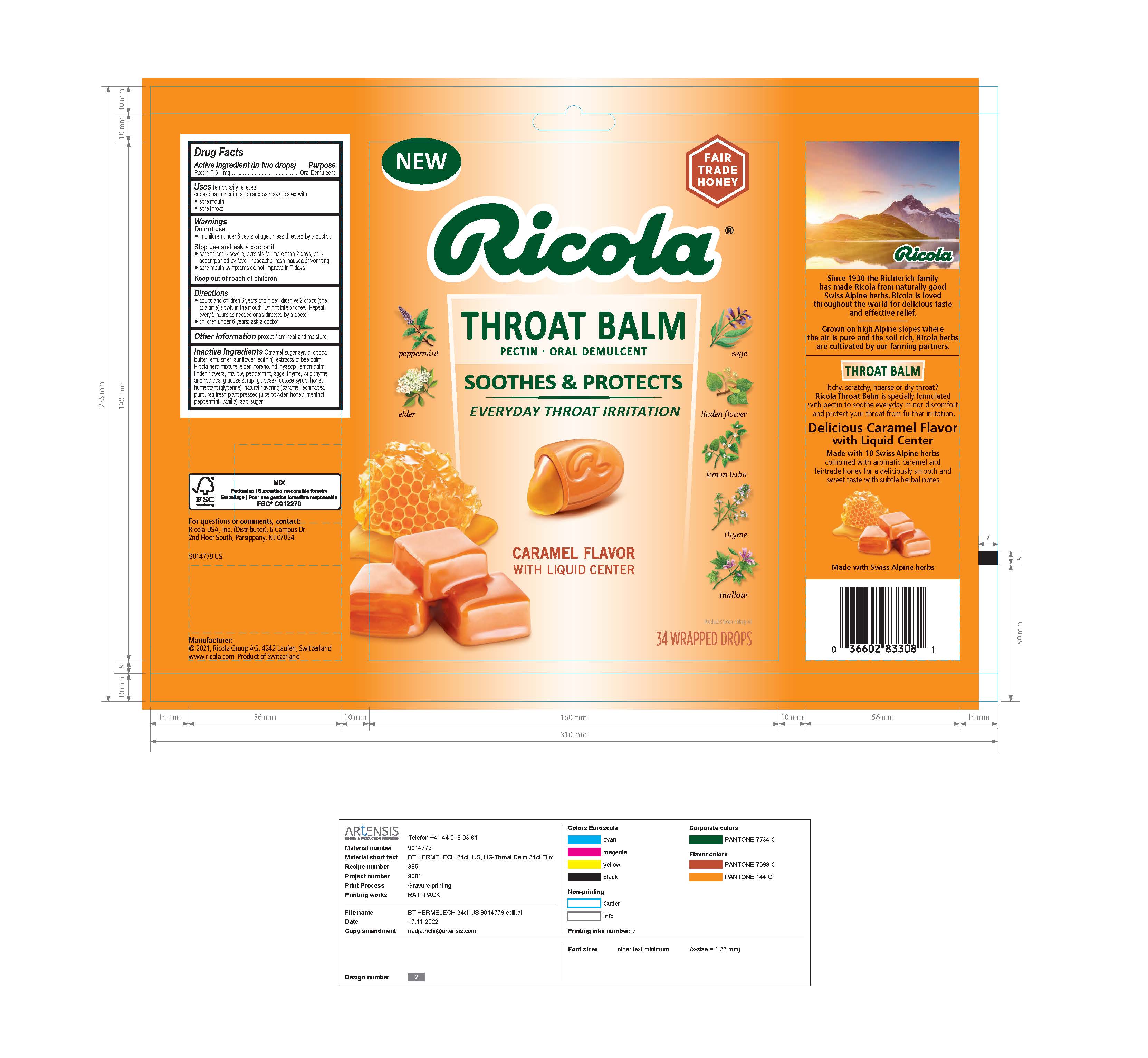 DRUG LABEL: Throat Balm Caramel Pectin
NDC: 63667-301 | Form: LOZENGE
Manufacturer: Ricola USA Inc.
Category: otc | Type: HUMAN OTC DRUG LABEL
Date: 20241210

ACTIVE INGREDIENTS: PECTIN 3.8 mg/1 1
INACTIVE INGREDIENTS: SUCROSE CARAMEL

Ricola Throat Balm Caramel Pectin

Active ingredient (in two drops)

Pectin 7.6 mg

Purpose

Oral demulcent

INDICATIONS AND USAGE

Uses temporarily relieves:

occasional minor irritation and pain associated with

- sore mouth
- sore throat

Warnings

Do not use

- in children under 6 years of age unless directed by a doctor.

Stop use and ask a doctor if

- sore throat is severe, persists for more than 2 days, or is accompanied by fever, headache, rash, nausea, or vomiting.
- sore mouth symptoms do not improve in 7 days.

Keep out of reach of children.

Directions

- adults and children 6 years and older: dissolve 2 drops (one at a time) slowly in the mouth. Do not bite or chew. Repeat every 2 hours as needed or as directed by a doctor
- children under 6 years: ask a doctor

Other Information

protect from heat and moisture

INACTIVE INGREDIENT

Inactive Ingredients: Caramel sugar syrup; cocoa butter; emulsifier (sunflower lecithin), extracts of bee balm, Ricola herb mixture (elder, horehound, hyssop, lemon balm, linden flowers, mallow, peppermint, sage, thyme, wild thyme) and rooibos; glucose syrup; glucose-fructose syrup; honey; humectant (glycerine); natural flavoring (caramel, echinacea purpurea fresh plant pressed juice powder, honey, menthol, peppermint, vanilla); salt; sugar